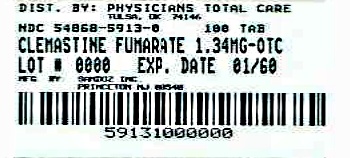 DRUG LABEL: Clemastine Fumarate
NDC: 54868-5913 | Form: TABLET
Manufacturer: Physicians Total Care, Inc.
Category: otc | Type: HUMAN OTC DRUG LABEL
Date: 20120521

ACTIVE INGREDIENTS: CLEMASTINE FUMARATE 1.34 mg/1 1
INACTIVE INGREDIENTS: LACTOSE MONOHYDRATE; STARCH, CORN; CELLULOSE, MICROCRYSTALLINE; HYPROMELLOSE 2910 (3 MPA.S); SODIUM STARCH GLYCOLATE TYPE A POTATO; MAGNESIUM STEARATE

Drug Facts

Active ingredient

Clemastine fumarate 1.34 mg (equivalent to 1 mg clemastine)

Purpose

Antihistamine

Keep out of reach of children.

In case of overdose, get medical help or contact a Poison Control Center right away.

Uses

Temporarily relieves these symptoms of the common cold, hay fever, or other upper respiratory allergies:

- runny nose
- itchy, watery eyes
- sneezing
- itching of the nose or throat

Warnings

Ask a doctor before use if you have

- glaucoma
- a breathing problem such as emphysema or chronic bronchitis
- trouble urinating due to an enlarged prostate gland

Ask a doctor or pharmacist before use if you are

taking sedatives or tranquilizers.

When using this product

- you may get drowsy
- avoid alcoholic drinks
- alcohol, sedatives, and tranquilizers may increase drowsiness
- be careful when driving a motor vehicle or operating machinery
- excitability may occur, especially in children

If pregnant or breast-feeding,

ask a health professional before use.

Directions

adults and children 12 years and older: | 1 tablet every 12 hours; not more than 2 tablets in 24 hours
children under 12 years: | ask a doctor

Other Information

- Safety sealed: do not use if the imprinted bottle seal is open or torn.
- Store at 20°-25°C (68°-77°F).

Inactive Ingredients

Hydroxypropyl methylcellulose, lactose (monohydrate), magnesium stearate, microcrystalline cellulose, sodium starch glycolate, and starch (corn).

Questions or comments?

1-800-525-8747

PRINCIPAL DISPLAY PANEL

NDC 54868-5913-0

Clemastine

Fumarate

Tablets, USP

1.34 mg

100 Tablets

Antihistamine

12 Hour Relief

Relief of: Sneezing Runny Nose

Itchy, Watery Eyes